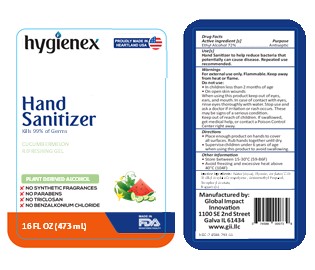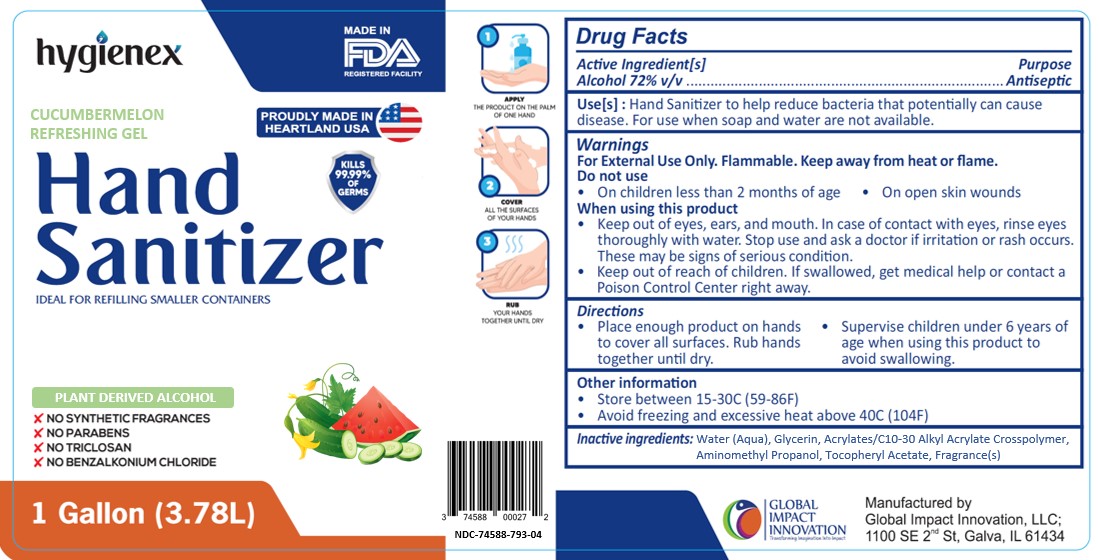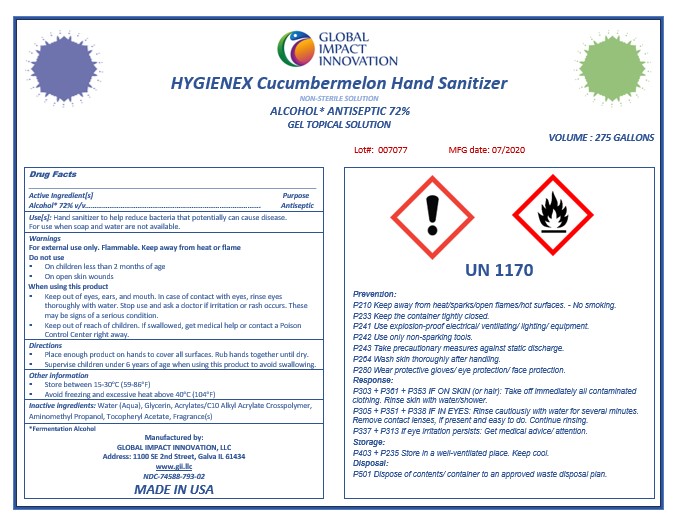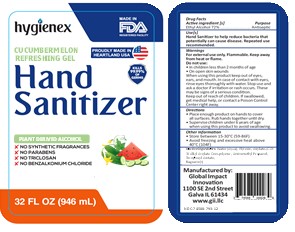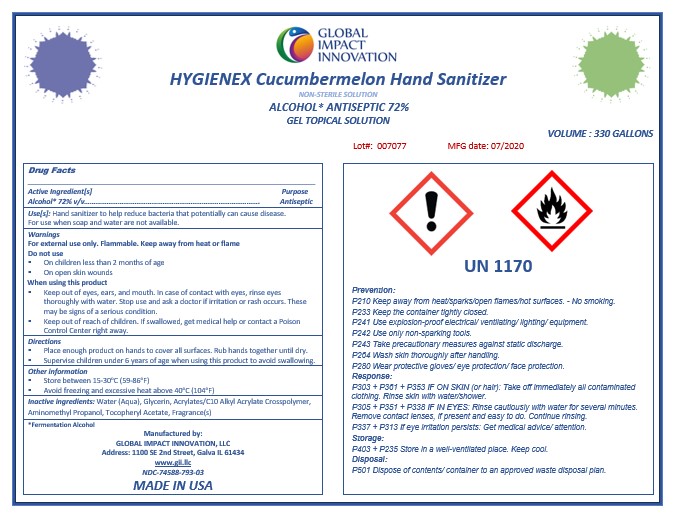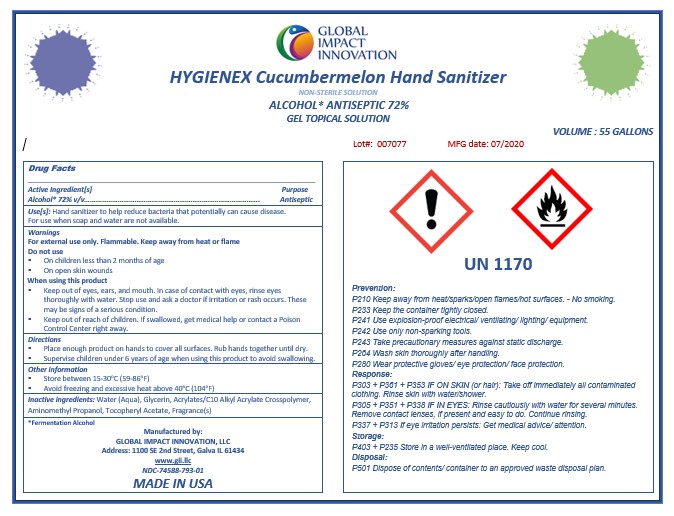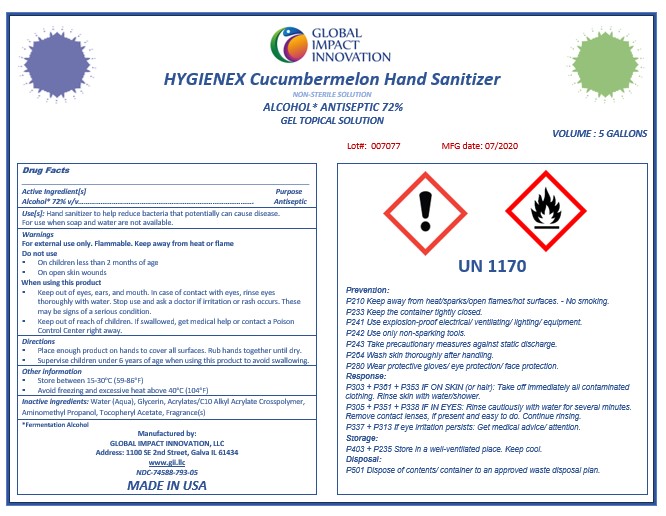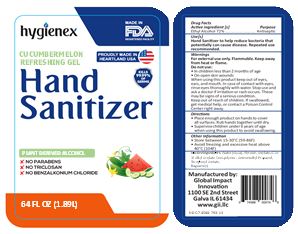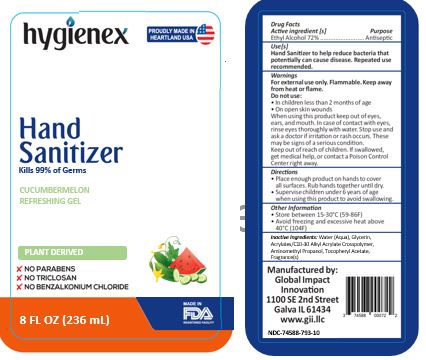 DRUG LABEL: Hygienex Cucumbermelon Hand Sanitizer
NDC: 74588-793 | Form: SOLUTION
Manufacturer: Global Impact Innovation LLC
Category: otc | Type: HUMAN OTC DRUG LABEL
Date: 20200923

ACTIVE INGREDIENTS: ALCOHOL 72 mL/100 mL
INACTIVE INGREDIENTS: .ALPHA.-TOCOPHEROL ACETATE; AMINOMETHYLPROPANOL; CARBOMER INTERPOLYMER TYPE A (55000 CPS); GLYCERIN; WATER

Active Ingredient(s)

Alcohol 72% v/v. Purpose: Antiseptic

Purpose

Antiseptic, Hand Sanitizer

Use

Hand Sanitizer to help reduce bacteria that potentially can cause disease. For use when soap and water are not available.

Warnings

For external use only. Flammable. Keep away from heat or flame

Do not use

- in children less than 2 months of age
- on open skin wounds

When using this product keep out of eyes, ears, and mouth. In case of contact with eyes, rinse eyes thoroughly with water.
Stop use and ask a doctor if irritation or rash occurs. These may be signs of a serious condition.
Keep out of reach of children. If swallowed, get medical help or contact a Poison Control Center right away.

Stop use and ask a doctor if irritation or rash occurs. These may be signs of a serious condition.

Keep out of reach of children. If swallowed, get medical help or contact a Poison Control Center right away.

Directions

- Place enough product on hands to cover all surfaces. Rub hands together until dry.
- Supervise children under 6 years of age when using this product to avoid swallowing.

Other information

- Store between 15-30C (59-86F)
- Avoid freezing and excessive heat above 40C (104F)

Inactive ingredients

glycerin, water, Acrylates/C10-30 Alkyl Acrylate Crosspolymer, AMP, Tocopherol Acetate, Fragrance(s)

Package Label - Principal Display Panel

1 Gallon NDC: 74588-793-04

5 Gallon NDC: 74588-793-05

55 Gallon NDC: 74588-793-01

275 Gallon NDC: 74588-793-02

330 Gallon NDC: 74588-793-03

16 Oz NDC: 74588-793-11

32 Oz NDC: 74588-793-12

64 Oz NDC: 74588-793-13

8 Oz NDC: 74588-793-10